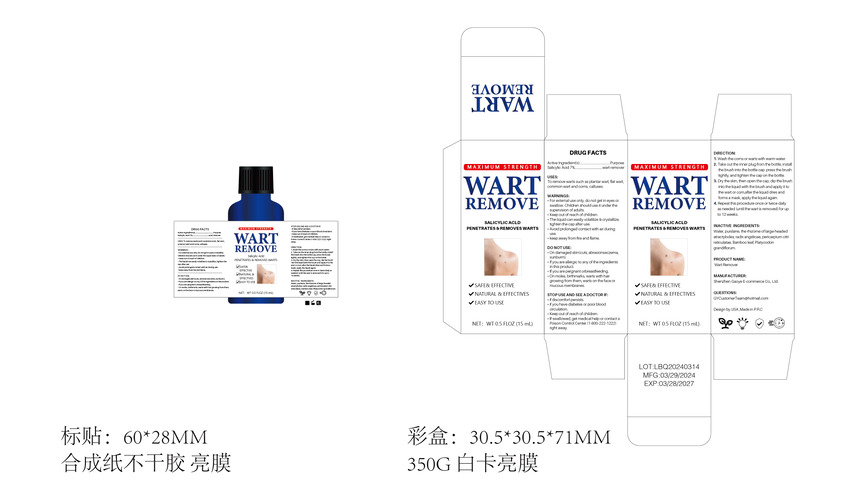 DRUG LABEL: WART REMOVE
NDC: 84322-002 | Form: LIQUID
Manufacturer: Shenzhen Gaoye E-commerce Co., Ltd
Category: otc | Type: HUMAN OTC DRUG LABEL
Date: 20240512

ACTIVE INGREDIENTS: SALICYLIC ACID 7 g/100 mL
INACTIVE INGREDIENTS: ANGELICA DAHURICA VAR. FORMOSANA WHOLE; PURSLANE; BAMBUSA VULGARIS LEAF; WATER; TANGERETIN

Active Ingredient(s)

salicylic acid-7%

Purpose

wart remover

Use

To remove warts such as plantar wart, flat wart, common wart and coms, calluses.

Warnings

●For external use only, do not get in eyes or swallow. Children should use it under the
supervision of adults.
●Keep out of reach of children.
●The liquid can easily volatilize 8 crystalize, tighten the cap after use.
●Avoid prolonged contact with air during use.
●keep away from fre and flame.

Do not use

●On damaged skin(cuts, abrasionseczema, sunburm).
●Ifyou are allergic to any of the ingredients in this product
●If you are pergnant orbrestfeeding.
●On moles, birthmarks, warts with hair growing from them, warts on the face or
mucous membranes.

When using this product keep out of eyes, ears, and mouth. In case of contact with eyes, rinse eyes thoroughly with water.

STOP USE

●if discomfort persists.
●if you have diabetes or poor blood circulation.
●Keep out of reach of children.
●If swallowed, get medical help or contact a Poison Control Center (1-800-222-1222) right away.

Keep out of reach of children. If swallowed, get medical help or contact a Poison Control Center right away.

Directions

1. Wash the corns or warts with warm water.
2. Take out the inner plug from the bottle, install the brush into the bottle cap. press the brush
tightly, and tighten the cap on the bottle.
3. Dry the skin, then open the cap, dip the brush into the liquid with the brush and apply it to
the wart or corn,after the liquid dries and forms a mask, apply the liquid again.
4. Repeat this procedure once or twice daily as needed (until the wart is removed) for up
to 12 weeks.

Other information

No data available

Inactive ingredients

Water, purslane, the rhizome of largeheaded atractylodes, radix angelicae, pericarpium citri
reticulatae, Bamboo leaf, Platycodon grandiflorum.